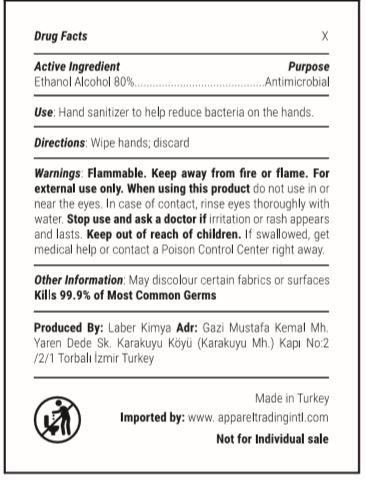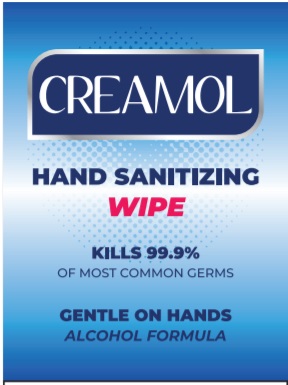 DRUG LABEL: wet wipes sanitizer
NDC: 77892-0004 | Form: SWAB
Manufacturer: LABER KIMYA AR-GE SANAYI TICARET - LEVENT KAHRIMAN
Category: otc | Type: HUMAN OTC DRUG LABEL
Date: 20200811

ACTIVE INGREDIENTS: ALCOHOL 80 g/100 g
INACTIVE INGREDIENTS: WATER; GLYCERIN; MELALEUCA ALTERNIFOLIA LEAF; HYPERICUM PERFORATUM LEAF

PURPOSE

Antibacterial

WARNINGS

For external use only.Keep out of the eyes. In case of eye contact, rinse with water.If irritation develps discontinue use and consult a doctor if irritation persists more than 72 hours. If swallowed, seek medical attention or contact a Poison Control Center.

INACTIVE INGREDIENT

Alcohol Denat (Ethanol) ,Glycerin, Melaleuca Alternifolia Leaf Extract, Hypericum Perforatum Extract, Chlorhexidine Gluconate , Aqua

ACTIVE INGREDIENT

% 80 Alcohol Denat (Ethanol)

INDICATIONS AND USAGE

ecreases bacteria on skin. recommended for repeated use

KEEP OUT OF REACH OF CHILDREN

Keep out of the reach of children, except with adult supervision.

DOSAGE AND ADMINISTRATION

ake wipe and rub thoroughly over all surfaces of both hands.Rrub hands together briskly to dry·dispose of wipe. For children under 2 years ask a doctor before use.